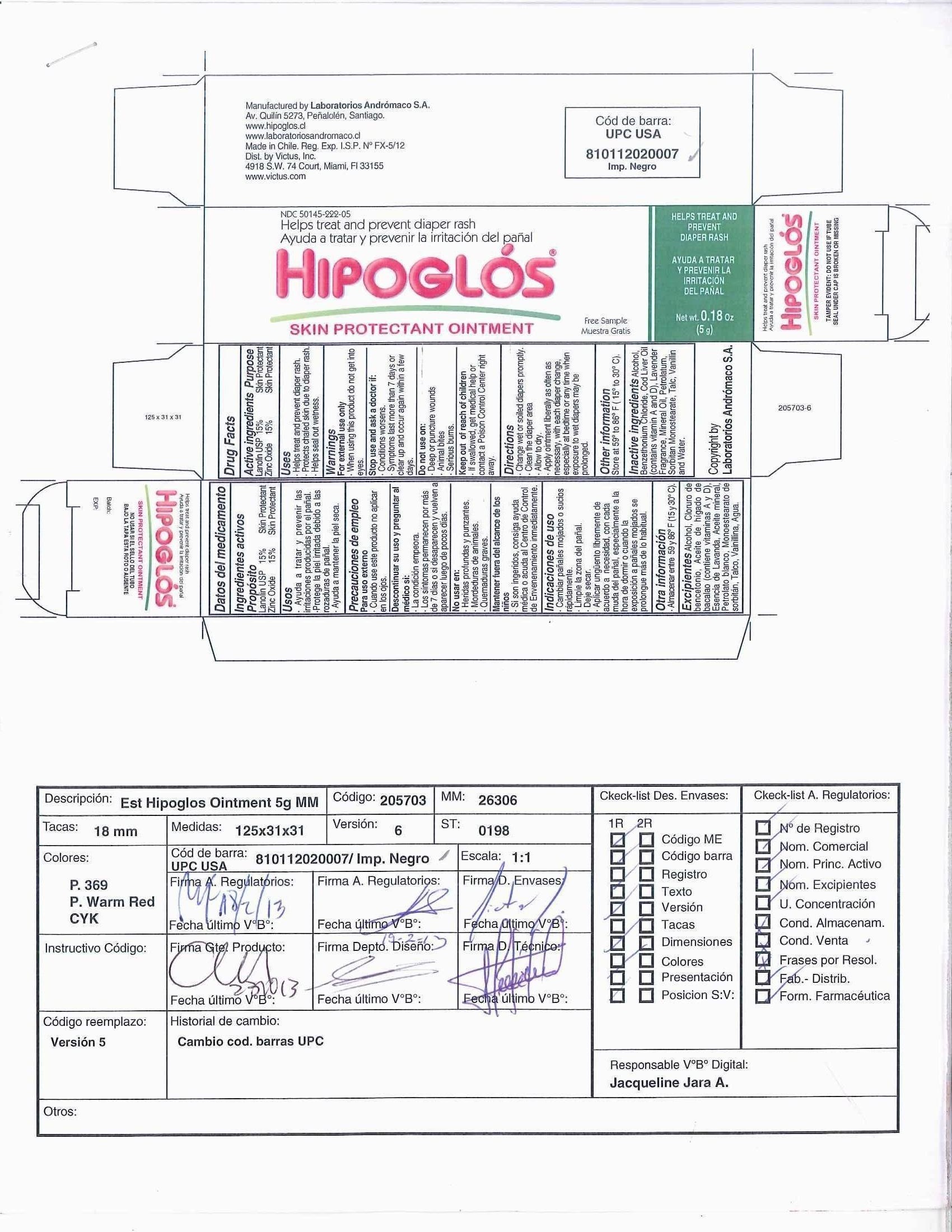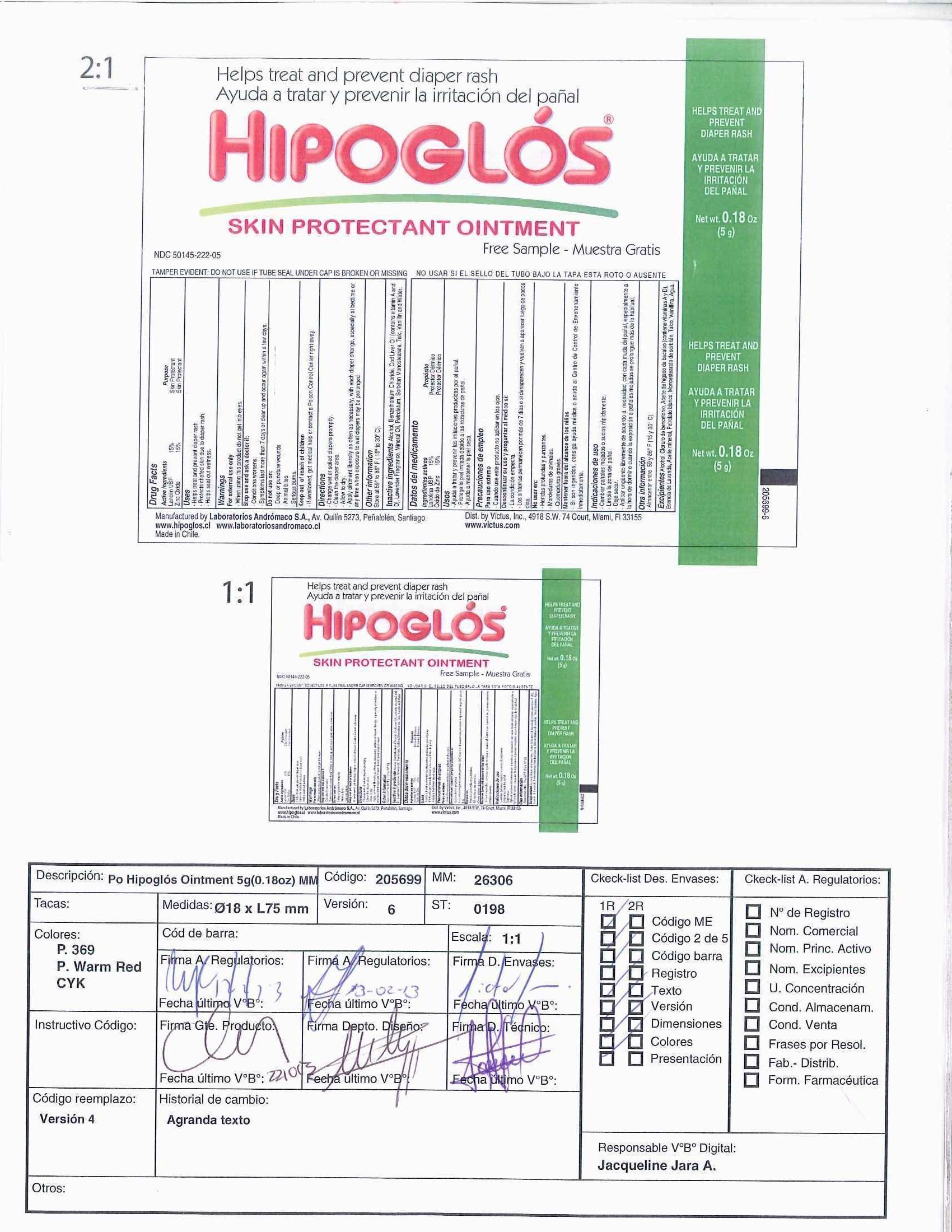 DRUG LABEL: Hipoglos
NDC: 50145-222 | Form: OINTMENT
Manufacturer: Laboratorios Andromaco S.A.
Category: otc | Type: HUMAN OTC DRUG LABEL
Date: 20131102

ACTIVE INGREDIENTS: ZINC OXIDE 15 g/100 g; LANOLIN 15 g/100 g
INACTIVE INGREDIENTS: ALCOHOL; BENZETHONIUM CHLORIDE; COD LIVER OIL; ENGLISH LAVENDER OIL; MINERAL OIL; PETROLATUM; SORBITAN MONOSTEARATE; TALC; VANILLIN; WATER

Hipoglós® Ointment

Active ingredient

Lanolin USP 15%

Zinc Oxide 15%

Purpose

Skin Protectant

Uses

- Helps treat and prevent diaper rash.
- Protects chafed skin due to diaper rash.
- Helps seal out wetness.

Warnings

For external use only

When using this product - do not get into eyes

Stop use and ask a doctor if:

- Conditions worsen.
- Symptoms last more than 7 days or clear up and occur again within a few days.

Do not use on:

- Deep or puncture wounds
- Animal Bites
- Serious Burns

Keep out of reach of children

- If swallowed, get medical help or contact a Poison Control Center right away.

Directions

- Change wet or soiled diapers promptly.
- Clean the diaper area.
- Allow to dry.
- Apply ointment liberally as often as necessary, with each diaper change, especially at bedtime or any time when exposure to wet diapers may be prolonged.

Other Information

Store at 59° to 86° F (15 ° to 30° C)

Inactive ingredients

Alcohol, Benzethonium Chloride, Cod Liver Oil (contains vitamin A and D), Lavender Fragrance, Mineral Oil, Petrolatum, Sorbitan Monostearate, Talc, Vanillin, and Water.

Propósito

Protector dérmico

Usos

- Ayuda a tratar y prevenir las irritaciones producidas por el pañal.
- Protege la piel irritada debido a las rozaduras de pañal.
- Ayuda a mantener la piel seca.

Warnings

Para uso externo
*Cuando use este producto no aplicar en los ojos.

Descontinuar su uso y preguntar al médico si:
• la condición empeora
• Los síntomas permanecen por más de 7 días o si desaparecen y vuelven a aparecer luego de pocos días.

No usar en:
• Heridas profundas y punzantes.
• Mordeduras de animales
• Quemaduras graves

Mantener fuera del alcance de los niños

* Si son ingeridos, consiga ayuda médica o acuda al Centro de Control de Envenenamiento inmediatamente.

Indicaciones de uso

- Cambiar pañales mojados o sucios rápidamente.
- Limpie la zona del pañal.
- Deje secar.
- Aplicar ungüento libremente de acuerdo a necesidad, con cada muda del pañal, especialmente a la hora de dormir o cuando la exposición a pañales mojados se prolongue más de lo habitual.

Otra información

*Almacenar entre 59° y 86° F (15 y 30°C).

Excipientes

alcohol, cloruro de bencetonio, aceite de hígado de bacalao (contiene vitaminas A y D), esencia de lavanda, aceite mineral, petrolato blanco, monoestearato de sorbitan, talco, vainillina, agua.

Principal Display Panel - Carton Label

Carton Label

Hipoglós® Ointment

Helps prevent and treat diaper rash, skin irritation

Net wt. 4.2 oz (120 g)

Principal Display Panel - Tube Label

Tube Label

Hipoglós® Ointment

Helps prevent and treat diaper rash, skin irritation

Net wt. 4.2 oz (120 g)